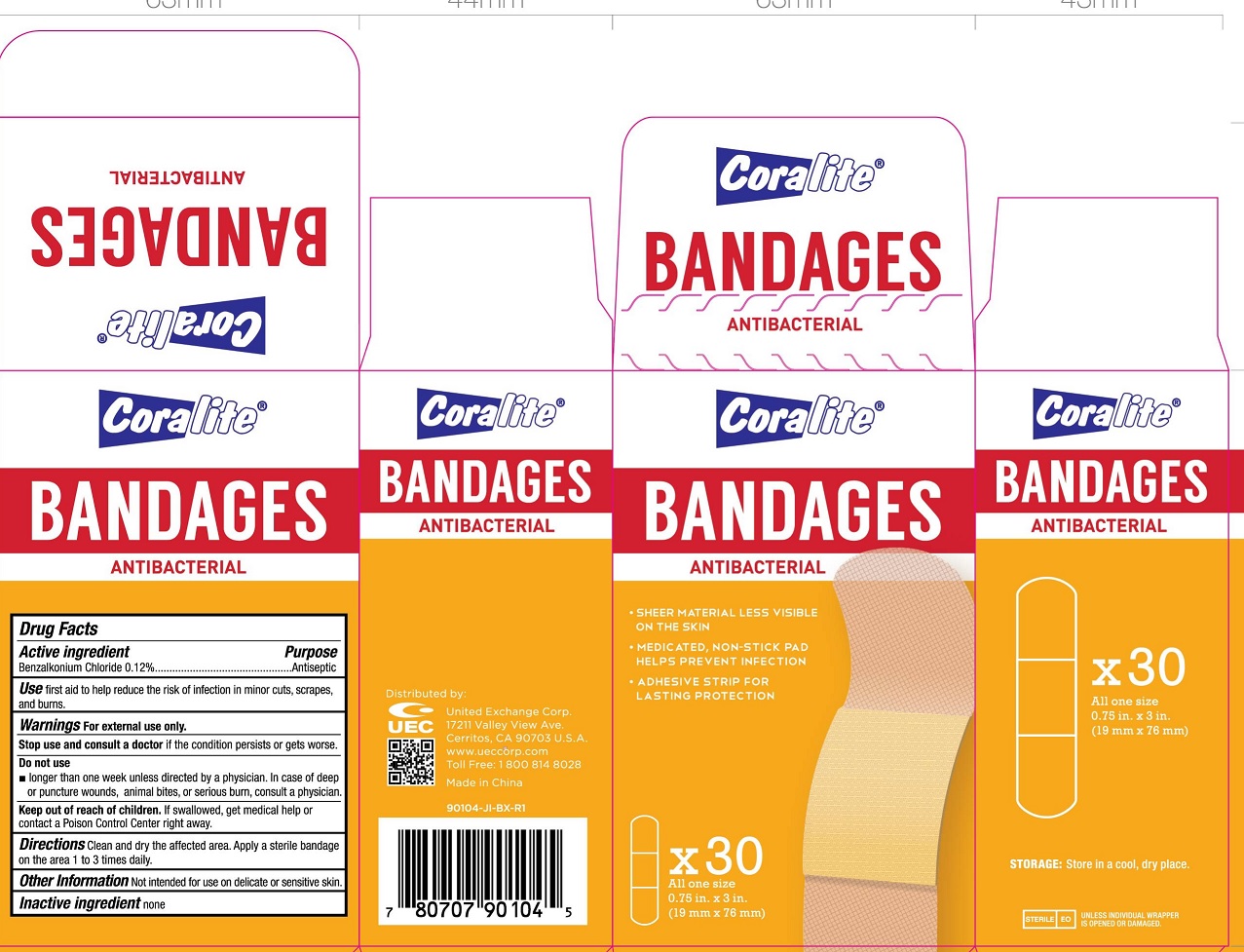 DRUG LABEL: coralite ANTIBACTERIAL BANDAGES
NDC: 69139-106 | Form: SWAB
Manufacturer: YIWU HAODING MEDICAL CO.,LTD
Category: otc | Type: HUMAN OTC DRUG LABEL
Date: 20230303

ACTIVE INGREDIENTS: BENZALKONIUM CHLORIDE 0.12 g/100 g
INACTIVE INGREDIENTS: WATER

Active Ingredients

Benzalkonium Chloride 0.12%

Purpose

Antiseptic

Use

First aid to help reduce the risk of infection in minor cuts ,scrapes,and burns.

Warnings

For external use only.

Stop use and consult a doctor if the condition persists or gets worse.

Do not use longer than 1 week unless directed by a physician. In case of deep or puncture wounds, animal bites, or serious burn, consult a physician.

Keep out of reach of children.if swallowed get medical help or contact Poison control Center right away.

Directions

Clean and dry the affected area. Apply a sterile bandage on the area 1 to 3 times daily.

Other information: not intended for use on delicate or sensitive skin.

Inactive Ingredient

None